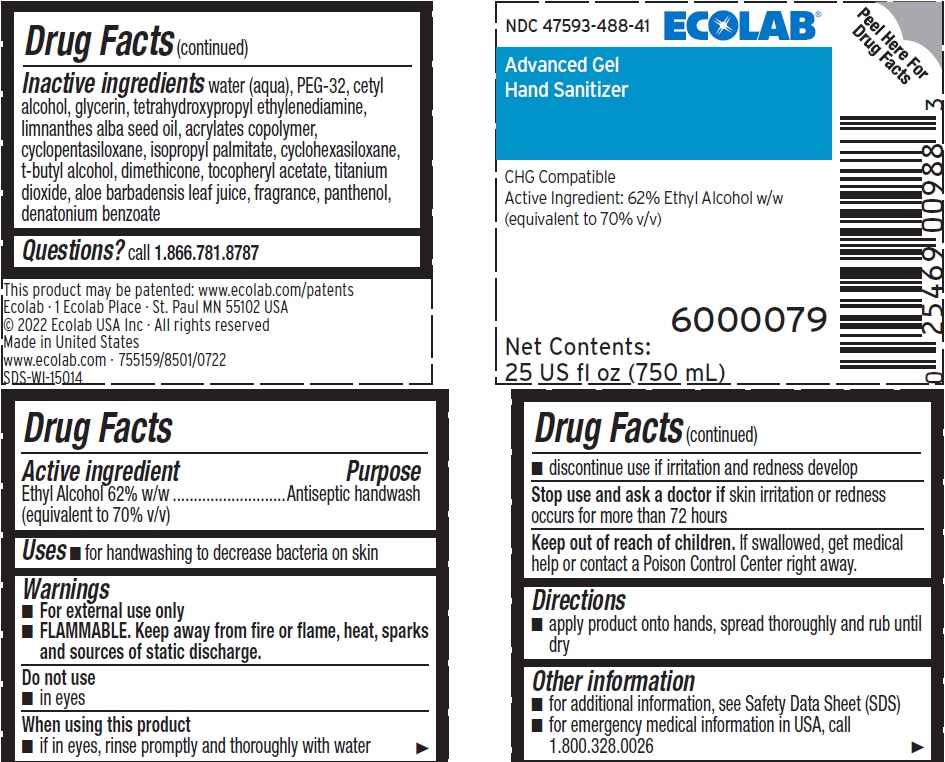 DRUG LABEL: Advanced Gel Hand Sanitizer
NDC: 47593-488 | Form: SOLUTION
Manufacturer: Ecolab Inc.
Category: otc | Type: HUMAN OTC DRUG LABEL
Date: 20251210

ACTIVE INGREDIENTS: ALCOHOL 70 mL/100 mL
INACTIVE INGREDIENTS: WATER; POLYETHYLENE GLYCOL 1500; CETYL ALCOHOL; GLYCERIN; EDETOL; MEADOWFOAM SEED OIL; CARBOMER INTERPOLYMER TYPE A (ALLYL SUCROSE CROSSLINKED); CYCLOMETHICONE 5; CYCLOMETHICONE 6; ISOPROPYL PALMITATE; TERT-BUTYL ALCOHOL; .ALPHA.-TOCOPHEROL ACETATE; DIMETHICONE; TITANIUM DIOXIDE; ALOE VERA LEAF; PANTHENOL; DENATONIUM BENZOATE

Drug Facts

Active ingredient

Ethyl Alcohol 62% w/w (equivalent to 70% v/v)

Purpose

Antiseptic handwash

Uses

- For handwashing to decrease bacteria on skin

Warnings

- For external use only
- FLAMMABLE. Keep away from fire or flame, heat, sparks and sources of static discharge.

Do not use

- In eyes

When using this product

- If in eyes, rinse promptly and thoroughly with water
- Discontinue use if irritation and redness develop

Stop use and ask a doctor if

Skin irritation or redness occurs for more than 72 hours

Keep out of reach of children. If swallowed, get medical help or contact a Poison Control Center right away.

Directions

- Apply product onto hands, spread thoroughly and rub until dry

Other information

- for additional information, see Safety Data Sheet (SDS)
- for emergency medical information in USA, call 1.800.328.0026

INACTIVE INGREDIENT

Inactive ingredients Water (Aqua), PEG-32, Cetyl Alcohol, Glycerin, Tetrahydroxypropyl Ethylenediamine, Limnanthes Alba Seed Oil , Acrylates Copolymer, Cyclopentasiloxane, Isopropyl Palmitate, Cyclohexasiloxane, t-Butyl Alcohol, Dimethicone, Tocopheryl Acetate, Titanium Dioxide, Aloe Barbadensis Leaf Juice, fragrance, Panthenol, Denatonium benzoate

Questions? call 1.866.781.8787

Representative label and principal display panel

NDC 47593-488-41 ECOLAB

Advanced Gel

Hand Sanitizer

CHG Compatible

Active Ingredient: 62% Ethyl Alcohol w/w

(equivalent to 70% v/v)

6000079

Net Contents:

25 US fl oz (750 mL)

This product may be patented: www.ecolab.com/patents

Ecolab · 1 Ecolab Place · St. Paul MN 55102 USA

© 2022 Ecolab USA Inc · All rights reserved

Made in United States

www.ecolab.com · 755159/8501/0722

SDS-WI-15014